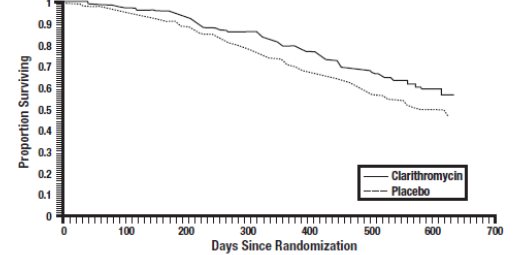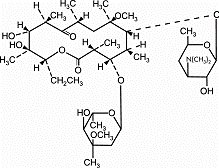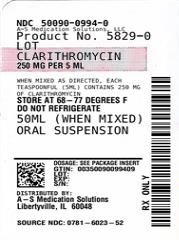 DRUG LABEL: Clarithromycin
NDC: 50090-0994 | Form: FOR SUSPENSION
Manufacturer: A-S Medication Solutions
Category: prescription | Type: HUMAN PRESCRIPTION DRUG LABEL
Date: 20260219

ACTIVE INGREDIENTS: CLARITHROMYCIN 250 mg/5 mL
INACTIVE INGREDIENTS: CITRIC ACID MONOHYDRATE; SAND; GLYCERYL MONOSTEARATE; HYDROXYPROPYL METHYLCELLULOSE; MALTODEXTRIN; POLYETHYLENE GLYCOL, UNSPECIFIED; POLYSORBATE 80; POTASSIUM SORBATE; POVIDONE; CI 77891; TRIETHYL CITRATE; XANTHAN GUM; SUCROSE; METHACRYLIC ACID AND ETHYL ACRYLATE COPOLYMER; POLOXAMER 188

HIGHLIGHTS OF PRESCRIBING INFORMATION

These highlights do not include all the information needed to use CLARITHROMYCIN FOR ORAL SUSPENSION safely and effectively. See full prescribing information for CLARITHROMYCIN FOR ORAL SUSPENSION.
CLARITHROMYCIN for oral suspension, for oral use
Initial U.S. Approval: 1991

RECENT MAJOR CHANGES

Contraindications (4) 05/2023

Drug Interactions (7) 05/2023

1 INDICATIONS AND USAGE

Clarithromycin is a macrolide antimicrobial indicated for mild to moderate infections caused by designated, susceptible bacteria in the following:

- Acute Bacterial Exacerbation of Chronic Bronchitis in Adults (1.1)
- Acute Maxillary Sinusitis (1.2)
- Community-Acquired Pneumonia (1.3)
- Pharyngitis/Tonsillitis (1.4)
- Uncomplicated Skin and Skin Structure Infections (1.5)
- Acute Otitis Media in Pediatric Patients (1.6)
- Treatment and Prophylaxis of Disseminated Mycobacterial Infections (1.7)

Limitations of Use:

To reduce the development of drug-resistant bacteria and maintain the effectiveness of clarithromycin and other antibacterial drugs, clarithromycin should be used only to treat or prevent infections that are proven or strongly suspected to be caused by bacteria. (1.9)

2 DOSAGE AND ADMINISTRATION

- Pediatric Patients: Clarithromycin 15 mg/kg/day divided every 12 hours for 10 days (2.4)
- Mycobacterial Infections: Clarithromycin 500 mg every 12 hours; Clarithromycin 7.5 mg/kg up to 500 mg every 12 hours in pediatric patients (2.5)
- Reduce dose in moderate renal impairment with concomitant atazanavir or ritonavir-containing regimens and in severe renal impairment (2.6)

3 DOSAGE FORMS AND STRENGTHS

- Granules for Oral Suspension: 125 mg/5 mL and 250 mg/5 mL (3)

4 CONTRAINDICATIONS

- Hypersensitivity to clarithromycin or any macrolide drug (4.1)
- Cisapride and pimozide (4.2)
- History of cholestatic jaundice/hepatic dysfunction with use of clarithromycin (4.3)
- Colchicine in renal or hepatic impairment (4.4)
- Lomitapide, lovastatin, and simvastatin (4.5)
- Ergot alkaloids (ergotamine or dihydroergotamine) (4.6)
- Lurasidone (4.7)

5 WARNINGS AND PRECAUTIONS

- Severe acute hypersensitivity reactions: Discontinue clarithromycin if occurs (5.1)
- QT prolongation: Avoid clarithromycin in patients with known QT prolongation or receiving drugs known to prolong the QT interval, ventricular arrhythmia (torsades de pointes), hypokalemia/hypomagnesemia, significant bradycardia, or taking Class IA or III antiarrhythmics (5.2)
- Hepatotoxicity: Discontinue if signs and symptoms of hepatitis occur (5.3)
- Serious adverse reactions can occur due to drug interactions of clarithromycin with colchicine, some lipid-lowering agents, some calcium channel blockers, and other drugs (5.4)
- Risk of all-cause mortality one year or more after the end of treatment in patients with coronary artery disease. Balance this potential risk with the treatment benefits when prescribing clarithromycin in these patients (5.5)
- Clostridium difficile associated diarrhea (CDAD): Evaluate if diarrhea occurs (5.6)
- Embryo-fetal Toxicity: Based on animal findings, clarithromycin is not recommended for use in pregnant women except in clinical circumstances where no alternative therapy is appropriate (5.7)
- Exacerbation of myasthenia gravis has been reported in patients receiving clarithromycin therapy (5.8)

6 ADVERSE REACTIONS

Most frequent adverse reactions for both adult and pediatric populations in clinical trials: abdominal pain, diarrhea, nausea, vomiting, dysgeusia (6.1)

To report SUSPECTED ADVERSE REACTIONS, contact Sandoz Inc. at 1-800-525-8747 or FDA at 1-800-FDA-1088 or www.fda.gov/medwatch.

7 DRUG INTERACTIONS

Co-administration of clarithromycin can alter the concentrations of other drugs. The potential for drug-drug interactions must be considered prior to and during therapy. (4, 5.2, 5.4, 7)

8 USE IN SPECIFIC POPULATIONS

Geriatric: Increased risk of torsades de pointes (8.5)

FULL PRESCRIBING INFORMATION

1 INDICATIONS AND USAGE

1.1 Acute Bacterial Exacerbation of Chronic Bronchitis

Clarithromycin is indicated in adults for the treatment of mild to moderate infections caused by susceptible isolates due to Haemophilus influenzae, Haemophilus parainfluenzae, Moraxella catarrhalis, or Streptococcus pneumoniae [see Indications and Usage (1.9)].

1.2 Acute Maxillary Sinusitis

Clarithromycin is indicated for the treatment of mild to moderate infections caused by susceptible isolates due to Haemophilus influenzae, Moraxella catarrhalis, or Streptococcus pneumoniae [see Indications and Usage (1.9)].

1.3 Community-Acquired Pneumonia

Clarithromycin is indicated [see Indications and Usage (1.9)] for the treatment of mild to moderate infections caused by susceptible isolates due to:

- Haemophilus influenzae (in adults)
- Mycoplasma pneumoniae, Streptococcus pneumoniae, Chlamydophila pneumoniae clarithromycin [in adults and pediatric patients]

1.4 Pharyngitis/Tonsillitis

Clarithromycin is indicated for the treatment of mild to moderate infections caused by susceptible isolates due to Streptococcus pyogenes as an alternative in individuals who cannot use first line therapy.

1.5 Uncomplicated Skin and Skin Structure Infections

Clarithromycin is indicated for the treatment of mild to moderate infections caused by susceptible isolates due to Staphylococcus aureus, or Streptococcus pyogenes.

1.6 Acute Otitis Media

Clarithromycin is indicated in pediatric patients for the treatment of mild to moderate infections caused by susceptible isolates due to Haemophilus influenzae, Moraxella catarrhalis, or Streptococcus pneumoniae [see Clinical Studies (14.2)].

1.7 Treatment and Prophylaxis of Disseminated Mycobacterial Infections

Clarithromycin is indicated for the treatment of mild to moderate infections caused by susceptible isolates due to Mycobacterium avium or Mycobacterium intracellulare in patients with advanced HIV infection [see Clinical Studies (14.1)].

1.9 Limitations of Use

There is resistance to macrolides in certain bacterial infections caused by Streptococcus pneumoniae and Staphylococcus aureus. Susceptibility testing should be performed when clinically indicated.

1.10 Usage

To reduce the development of drug-resistant bacteria and maintain the effectiveness of clarithromycin and other antibacterial drugs, clarithromycin should be used only to treat or prevent infections that are proven or strongly suspected to be caused by susceptible bacteria. When culture and susceptibility information are available, they should be considered in selecting or modifying antibacterial therapy. In the absence of such data, local epidemiology and susceptibility patterns may contribute to the empiric selection of therapy.

2 DOSAGE AND ADMINISTRATION

2.1 Important Administration Instructions

Clarithromycin for oral suspension may be given with or without food.

2.4 Pediatric Dosage

The recommended daily dosage is 15 mg/kg/day divided every 12 hours for 10 days (up to the adult dose). Refer to dosage regimens for mycobacterial infections in pediatric patients for additional dosage information [see Dosage and Administration (2.5)].

2.5 Dosage Regimens for Mycobacterial Infections

For the treatment of disseminated infection due to Mycobacterium avium complex (MAC), clarithromycin is recommended as the primary agents. Clarithromycin should be used in combination with other antimycobacterial drugs (e.g. ethambutol) that have shown in vitro activity against MAC or clinical benefit in MAC treatment [see Clinical Studies (14.1)].

Adult Patients

For treatment and prophylaxis of mycobacterial infections in adults, the recommended dose of clarithromycin is 500 mg every 12 hours.

Pediatric Patients

For treatment and prophylaxis of mycobacterial infections in pediatric patients, the recommended dose is 7.5 mg/kg every 12 hours up to 500 mg every 12 hours. [see Use in Specific Populations (8.4) and Clinical Studies (14.1)].

Clarithromycin therapy should continue if clinical response is observed. Clarithromycin can be discontinued when the patient is considered at low risk of disseminated infection.

2.6 Dosage Adjustment in Patients with Renal Impairment

See Table 2 for dosage adjustment in patients with moderate or severe renal impairment with or without concomitant atazanavir or ritonavir-containing regimens [see Drug Interactions (7)].

Table 2. Clarithromycin Dosage Adjustments in Patients with Renal Impairment

 | Recommended ClarithromycinDosage Reduction
Patients with severe renal impairment (CLcr of <30 mL/min) | Reduce the dosage of Clarithromycin by 50%
Patients with moderate renal impairment (CLcr of 30 to 60 mL/min) taking concomitant atazanavir or ritonavir-containing regimens | Reduce the dosage of Clarithromycin by 50%
Patients with severe renal impairment (CLcr of <30 mL/min) taking concomitant atazanavir or ritonavir-containing regimens | Reduce the dosage of Clarithromycin by 75%

2.7 Dosage Adjustment Due to Drug Interactions

Decrease the dose of clarithromycin by 50 % when co-administered with atazanavir [see Drug Interactions (7)]. Dosage adjustments for other drugs when co-administered with clarithromycin may be recommended due to drug interactions [see Drug Interactions (7)].

2.8 Reconstitution of Clarithromycin for Oral Suspension

The supplied clarithromycin granules must be reconstituted with water prior to administration of clarithromycin for oral suspension. Table 3 below indicates the volume of water to be added when reconstituting. To reconstitute:

a. Add half the volume of water to the bottle containing the clarithromycin granules and shake vigorously.
b. Add the remainder of water to the bottle and shake.

Shake well before each use. After mixing, store at 15° to 30°C (59° to 86°F) and use within

14 days. Do not refrigerate.

Table 3. Volume of Water to be Added When Reconstituting Clarithromycin Granules

Total Volume After Reconstitution | Clarithromycin Concentration After Reconstitution | Amount of Water to be Added
50 mL | 125 mg/5 mL | 29.5 mL
100 mL | 125 mg/5 mL | 59 mL
50 mL | 250 mg/5 mL | 28.5 mL
100 mL | 250 mg/5 mL | 57 mL

3 DOSAGE FORMS AND STRENGTHS

Clarithromycin is available as:

• Clarithromycin for oral suspension (white to off-white granules before reconstitution; white to off-white opaque suspension after reconstitution):
◦ 125 mg/5 mL concentration available in 50 mL and 100 mL bottles
◦ 250 mg/5 mL concentration available in 50 mL and 100 mL bottles

4 CONTRAINDICATIONS

4.1 Hypersensitivity

Clarithromycin is contraindicated in patients with a known hypersensitivity to clarithromycin, erythromycin, or any of the macrolide antibacterial drugs [see Warnings and Precautions (5.1)].

4.2 Cisapride and Pimozide

Concomitant administration of clarithromycin with cisapride and pimozide is contraindicated [see Drug Interactions (7)].

There have been postmarketing reports of drug interactions when clarithromycin is co‑ administered with cisapride or pimozide, resulting in cardiac arrhythmias (QT prolongation, ventricular tachycardia, ventricular fibrillation, and torsades de pointes) most likely due to inhibition of metabolism of these drugs by clarithromycin. Fatalities have been reported.

4.3 Cholestatic Jaundice/Hepatic Dysfunction

Clarithromycin is contraindicated in patients with a history of cholestatic jaundice or hepatic dysfunction associated with prior use of clarithromycin.

4.4 Colchicine

Concomitant administration of clarithromycin and colchicine is contraindicated in patients with renal or hepatic impairment.

4.5 Lomitapide, Lovastatin, and Simvastatin

Concomitant administration of clarithromycin with lomitapide is contraindicated due to potential for markedly increased transaminases [see Warnings and Precautions (5.4) and Drug Interactions (7)].

Concomitant administration of clarithromycin with HMG-CoA reductase inhibitors (statins) that are extensively metabolized by CYP3A4 (lovastatin or simvastatin) is contraindicated, due to the increased risk of myopathy, including rhabdomyolysis [see Warnings and Precautions (5.4) and Drug Interactions (7)].

4.6 Ergot Alkaloids

Concomitant administration of clarithromycin and ergotamine or dihydroergotamine is contraindicated [see Drug Interactions (7)].

4.7 Lurasidone

Concomitant administration of clarithromycin and lurasidone is contraindicated since it may result in an increase in lurasidone exposure and the potential for serious adverse reactions [see Drug Interactions (7)].

4.8 Contraindications for Co-administered Drugs

For information about contraindications of other drugs indicated in combination with clarithromycin, refer to their full prescribing information (contraindications section).

5 WARNINGS AND PRECAUTIONS

5.1 Severe Acute Hypersensitivity Reactions

In the event of severe acute hypersensitivity reactions, such as anaphylaxis, Stevens-Johnson Syndrome, toxic epidermal necrolysis, drug rash with eosinophilia and systemic symptoms (DRESS), Henoch-Schonlein purpura, and acute generalized exanthematous pustulosis, discontinue clarithromycin therapy immediately and institute appropriate treatment.

5.2 QT Prolongation

- Clarithromycin has been associated with prolongation of the QT interval and infrequent cases of arrhythmia. Cases of torsades de pointes have been spontaneously reported during postmarketing surveillance in patients receiving clarithromycin. Fatalities have been reported.

Avoid clarithromycin in the following patients:

- patients with known prolongation of the QT interval, ventricular cardiac arrhythmia, including torsades de pointes
- patients receiving drugs known to prolong the QT interval [seealso Contraindications (4.2)]
- patients with ongoing proarrhythmic conditions such as uncorrected hypokalemia or hypomagnesemia, clinically significant bradycardia and in patients receiving Class IA (e.g., quinidine, procainamide, disopyramide) or Class III (e.g., dofetilide, amiodarone, sotalol) antiarrhythmic agents.

Elderly patients may be more susceptible to drug-associated effects on the QT interval [see Use in Specific Populations (8.5)].

5.3 Hepatotoxicity

Hepatic dysfunction, including increased liver enzymes, and hepatocellular and/or cholestatic hepatitis, with or without jaundice, has been reported with clarithromycin. This hepatic dysfunction may be severe and is usually reversible. In some instances, hepatic failure with fatal outcome has been reported and generally has been associated with serious underlying diseases and/or concomitant medications. Symptoms of hepatitis can include anorexia, jaundice, dark urine, pruritus, or tender abdomen. Discontinue clarithromycin immediately if signs and symptoms of hepatitis occur.

5.4 Serious Adverse Reactions Due to Concomitant Use with Other Drugs

Drugs metabolized by CYP3A4: Serious adverse reactions have been reported in patients taking clarithromycin concomitantly with CYP3A4 substrates. These include colchicine toxicity with colchicine; markedly increased transaminases with lomitapide; rhabdomyolysis with simvastatin, lovastatin, and atorvastatin; hypoglycemia and cardiac arrhythmias (e.g., torsades de pointes) with disopyramide; and hypotension and acute kidney injury with calcium channel blockers metabolized by CYP3A4 (e.g., verapamil, amlodipine, diltiazem, nifedipine). Most reports of acute kidney injury with calcium channel blockers metabolized by CYP3A4 involved elderly patients 65 years of age or older. Use clarithromycin with caution when administered concurrently with medications that induce the cytochrome CYP3A4 enzyme. The use of clarithromycin with lomitapide, simvastatin, lovastatin, ergotamine, or dihydroergotamine is contraindicated [see Contraindications (4.5, 4.6) and Drug Interactions (7)].

Colchicine: Life-threatening and fatal drug interactions have been reported in patients treated with clarithromycin and colchicine. Clarithromycin is a strong CYP3A4 inhibitor and this interaction may occur while using both drugs at their recommended doses. If co-administration of clarithromycin and colchicine is necessary in patients with normal renal and hepatic function, reduce the dose of colchicine. Monitor patients for clinical symptoms of colchicine toxicity. Concomitant administration of clarithromycin and colchicine is contraindicated in patients with renal or hepatic impairment [see Contraindications (4.4) and Drug Interactions (7)].

Lomitapide: Concomitant use of clarithromycin with lomitapide is contraindicated [see Contraindications (4.5)]. Lomitapide is metabolized by CYP3A4, and concomitant treatment with clarithromycin increases the plasma concentration of lomitapide, which increases the risk of elevation in transaminases [see Drug Interactions (7)]. If treatment with clarithromycin cannot be avoided, therapy with lomitapide must be suspended during the course of treatment.

HMG-CoA Reductase Inhibitors (statins): Concomitant use of clarithromycin with lovastatin or simvastatin is contraindicated [see Contraindications (4.5)] as these statins are extensively metabolized by CYP3A4, and concomitant treatment with clarithromycin increases their plasma concentration, which increases the risk of myopathy, including rhabdomyolysis. Cases of rhabdomyolysis have been reported in patients taking clarithromycin concomitantly with these statins. If treatment with clarithromycin cannot be avoided, therapy with lovastatin or simvastatin must be suspended during the course of treatment.

Exercise caution when prescribing clarithromycin with atorvastatin or pravastatin. In situations where the concomitant use of clarithromycin with atorvastatin or pravastatin cannot be avoided, atorvastatin dose should not exceed 20 mg daily and pravastatin dose should not exceed 40 mg daily. Use of a statin that is not dependent on CYP3A metabolism (e.g. fluvastatin) can be considered. It is recommended to prescribe the lowest registered dose if concomitant use cannot be avoided.

Oral Hypoglycemic Agents/Insulin: The concomitant use of clarithromycin and oral hypoglycemic agents and/or insulin can result in significant hypoglycemia. With certain hypoglycemic drugs such as nateglinide, pioglitazone, repaglinide and rosiglitazone, inhibition of CYP3A enzyme by clarithromycin may be involved and could cause hypoglycemia when used concomitantly. Careful monitoring of glucose is recommended [see Drug Interactions (7)].

Quetiapine: Use quetiapine and clarithromycin concomitantly with caution. Co-administration could result in increased quetiapine exposure and quetiapine related toxicities such as somnolence, orthostatic hypotension, altered state of consciousness, neuroleptic malignant syndrome, and QT prolongation. Refer to quetiapine prescribing information for recommendations on dose reduction if co-administered with CYP3A4 inhibitors such as clarithromycin [see Drug Interactions (7)].

Oral Anticoagulants: There is a risk of serious hemorrhage and significant elevations in INR and prothrombin time when clarithromycin is co-administered with warfarin. Monitor INR and prothrombin times frequently while patients are receiving clarithromycin and oral anticoagulants concurrently [see Drug Interactions (7)].

Benzodiazepines: Increased sedation and prolongation of sedation have been reported with concomitant administration of clarithromycin and triazolobenzodiazepines, such as triazolam and midazolam [see Drug Interactions (7)].

5.5 All-Cause Mortality in Patients with Coronary Artery Disease 1 to 10 Years after Clarithromycin Exposure

In one clinical trial evaluating treatment with clarithromycin on outcomes in patients with coronary artery disease, an increase in risk of all-cause mortality one year or more after the end of treatment was observed in patients randomized to receive clarithromycin.^1 Clarithromycin for treatment of coronary artery disease is not an approved indication. The cause of the increased risk has not been established. Other epidemiologic studies evaluating this risk have shown variable results [see Adverse Reactions (6.1)]. Consider balancing this potential risk with the treatment benefits when prescribing clarithromycin in patients who have suspected or confirmed coronary artery disease.

5.6 Clostridium difficile Associated Diarrhea

Clostridium difficile associated diarrhea (CDAD) has been reported with use of nearly all antibacterial agents, including clarithromycin, and may range in severity from mild diarrhea to fatal colitis. Treatment with antibacterial agents alters the normal flora of the colon leading to overgrowth of C. difficile.

C. difficile produces toxins A and B which contribute to the development of CDAD. Hypertoxin producing strains of C. difficile cause increased morbidity and mortality, as these infections can be refractory to antimicrobial therapy and may require colectomy. CDAD must be considered in all patients who present with diarrhea following antibacterial use. Careful medical history is necessary since CDAD has been reported to occur over two months after the administration of antibacterial agents.

If CDAD is suspected or confirmed, ongoing antibacterial use not directed against C. difficile may need to be discontinued. Appropriate fluid and electrolyte management, protein supplementation, antibacterial treatment of C. difficile, and surgical evaluation should be instituted as clinically indicated.

5.7 Embryo-fetal Toxicity

Based on findings from animal studies, clarithromycin is not recommended for use in pregnant women except in clinical circumstances where no alternative therapy is appropriate. If clarithromycin is used during pregnancy, or if pregnancy occurs while the patient is taking this drug, the patient should be apprised of the potential hazard to the fetus. Clarithromycin demonstrated adverse effects on pregnancy outcome and/or embryo- fetal development, including fetal malformations, in pregnant animals administered oral clarithromycin [see Use in Specific Populations (8.1)].

5.8 Exacerbation of Myasthenia Gravis

Exacerbation of symptoms of myasthenia gravis and new onset of symptoms of myasthenic syndrome has been reported in patients receiving clarithromycin therapy.

5.9 Development of Drug Resistant Bacteria

Prescribing clarithromycin in the absence of a proven or strongly suspected bacterial infection or a prophylactic indication is unlikely to provide benefit to the patient and increases the risk of the development of drug-resistant bacteria.

6 ADVERSE REACTIONS

The following serious adverse reactions are described below and elsewhere in the labeling:

- Acute Hypersensitivity Reactions [see Warnings and Precautions (5.1)]
- QT Prolongation [see Warnings and Precautions (5.2)]
- Hepatotoxicity [see Warnings and Precautions (5.3)]
- Serious Adverse Reactions Due to Concomitant Use with Other Drugs [see Warnings andPrecautions (5.4)]
- Clostridium difficile Associated Diarrhea [see Warnings and Precautions (5.6)]
- Exacerbation of Myasthenia Gravis [see Warnings and Precautions (5.8)]

6.1 Clinical Trials Experience

Because clinical studies are conducted under widely varying conditions, adverse reaction rates observed in the clinical studies of a drug cannot be directly compared to rates in the clinical studies of another drug and may not reflect the rates observed in practice.

Based on pooled data across all indications, the most frequent adverse reactions for both adult and pediatric populations observed in clinical trials are abdominal pain, diarrhea, nausea, vomiting and dysgeusia. Also reported were dyspepsia, liver function test abnormal, anaphylactic reaction, candidiasis, headache, insomnia, and rash.

The subsequent subsections list the most common adverse reactions for prophylaxis and treatment of mycobacterial infections and duodenal ulcer associated with H. pylori infection. In general, these profiles are consistent with the pooled data described above.

Prophylaxis of Mycobacterial Infections

In AIDS patients treated with clarithromycin over long periods of time for prophylaxis against M. avium, it was often difficult to distinguish adverse reactions possibly associated with clarithromycin administration from underlying HIV disease or intercurrent illness. Median duration of treatment was 10.6 months for the clarithromycin group and 8.2 months for the placebo group.

Table 4. Incidence Rates (%) of Selected Adverse Reactions*in Immunocompromised Adult Patients Receiving Prophylaxis Against M. avium Complex

Body System† Adverse Reaction | Clarithromycin (n=339) % | Placebo (n=339) %
Body as a Whole
Abdominal pain | 5% | 4%
Headache | 3% | 1%
Digestive
Diarrhea | 8% | 4%
Dyspepsia | 4% | 3%
Flatulence | 2% | 1%
Nausea | 11% | 7%
Vomiting | 6% | 3%
Skin & Appendages
Rash | 3% | 4%
Special Senses
Taste Perversion | 8%‡ | 0.3%

Discontinuation due to adverse reactions occurred in 18% of patients receiving clarithromycin compared to 17% of patients receiving placebo in this trial. Primary reasons for discontinuation in clarithromycin treated patients include headache, nausea, vomiting, depression, and taste perversion.

Changes in Laboratory Values

Selected laboratory adverse experiences that were reported during therapy in greater than 2 % of adult patients treated with clarithromycin in a randomized double-blind clinical trial involving 682 patients are presented in Table 5.

In immunocompromised patients receiving prophylaxis against M. avium, evaluations of laboratory values were made by analyzing those values outside the seriously abnormal value (i.e., the extreme high or low limit) for the specified test.

Table 5. Percentage of Patients* Exceeding Extreme Laboratory Values in Patients Receiving Prophylaxis Against M. avium Complex

 |  | Clarithromycin 500 mg; twice a day | Placebo
WBC Count | <1 x 10^9/L | 2/103 (4%) | 0/95
SGOT | >5 x ULN† | 7/196 (4%) | 5/208 (2%)
SGPT | >5 x ULN† | 6/217 (3%) | 4/232 (2%)
* Includes only patients with baseline values within the normal range or borderline high (hematology variables) and within normal range or borderline low (chemistry variables)
† ULN= Upper Limit of Normal

Treatment of Mycobacterial Infections

The adverse reaction profiles for both the 500 mg and 1000 mg twice a day dose regimens were similar.

In AIDS patients and other immunocompromised patients treated with the higher doses of clarithromycin over long periods of time for mycobacterial infections, it was often difficult to distinguish adverse reactions possibly associated with clarithromycin administration from underlying signs of HIV disease or intercurrent illness.

The following analysis summarizes experience during the first 12 weeks of therapy with clarithromycin. Data are reported separately for trial 1 (randomized, double-blind) and trial 2 (open‑ labeled, compassionate use) and also combined. Adverse reactions were reported less frequently in trial 2, which may be due in part to differences in monitoring between the two studies.

In adult patients receiving clarithromycin 500 mg twice a day, the most frequently reported adverse reactions, considered possibly or possibly related to study drug, with an incidence of 5% or greater, are listed below (Table 6). Approximately 8% of the patients who received 500 mg twice a day and 12% of the patients who received 1000 mg twice a day discontinued therapy due to drug related adverse reactions during the first 12 weeks of therapy; adverse reactions leading to discontinuation in at least 2 patients included nausea, vomiting, abdominal pain, diarrhea, rash, and asthenia.

Table 6. Selected Treatment-Related* Adverse Reaction Incidence Rates (%) in Immunocompromised Adult Patients During the First 12 Weeks of Therapy with 500 mg Twice a Day Clarithromycin Dose

Adverse Reaction | Trial 1; (n=53) | Trial 2; (n=255) | Combined; (n=308)
Abdominal Pain | 8 | 2 | 3
Diarrhea | 9 | 2 | 3
Flatulence | 8 | 0 | 1
Headache | 8 | 0 | 2
Nausea | 28 | 9 | 12
Rash | 9 | 2 | 3
Taste Perversion | 19 | 0 | 4
Vomiting | 25 | 4 | 8
* Includes those events possibly or probably related to study drug and excludes concurrent conditions

A limited number of pediatric AIDS patients have been treated with clarithromycin suspension for mycobacterial infections. The most frequently reported adverse reactions excluding those due to the patient’s concurrent conditions were consistent with those observed in adult patients.

Changes in Laboratory Values

In the first 12 weeks of starting on clarithromycin 500 mg twice a day, 3% of patients has SGOT increases and 2% of patients has SGPT increases >5 times the upper limit of normal in trial 2 (469 enrolled adult patients) while trial 1 (154 enrolled patients) had no elevation of transaminases. This includes only patients with baseline values within the normal range or borderline low.

Duodenal ulcer associated with H. pylori Infection

In clinical trials using combination therapy with clarithromycin plus omeprazole and amoxicillin, no adverse reactions specific to the combination of these drugs have been observed. Adverse reactions that have occurred have been limited to those that have been previously reported with clarithromycin, omeprazole or amoxicillin.

The adverse reaction profiles are shown below (Table 7) for four randomized double-blind clinical trials in which patients received the combination of clarithromycin 500 mg three times a day, and omeprazole 40 mg daily for 14 days, followed by omeprazole 20 mg once a day, (three studies) or 40 mg once a day (one study) for an additional 14 days. Of the 346 patients who received the combination, 3.5% of patients discontinued drug due to adverse reactions.

Table 7. Adverse Reactions with an Incidence of 3% or Greater

Adverse Reaction | Clarithromycin + Omeprazole; (n=346); % of Patients | Omeprazole; (n=355); % of Patients | Clarithromycin (n=166); % of Patients*
Taste Perversion | 15 | 1 | 16
Nausea | 5 | 1 | 3
Headache | 5 | 6 | 9
Diarrhea | 4 | 3 | 7
Vomiting | 4 | <1 | 1
Abdominal Pain | 3 | 2 | 1
Infection | 3 | 4 | 2

*Only two of four studies

Changes in Laboratory Values

Changes in laboratory values with possible clinical significance in patients taking clarithromycin and omeprazole in four randomized double-blind trials in 945 patients are as follows:

Hepatic: elevated direct bilirubin <1%; GGT <1%; SGOT (AST) <1%; SGPT (ALT) <1%.

Renal: elevated serum creatinine <1%.

Less Frequent Adverse Reactions Observed During Clinical Trials of Clarithromycin

Based on pooled data across all indications, the following adverse reactions were observed in clinical trials with clarithromycin at a rate less than 1%:

Blood and Lymphatic System Disorders: Leukopenia, neutropenia, thrombocythemia, eosinophilia

Cardiac Disorders: Electrocardiogram QT prolonged, cardiac arrest, atrial fibrillation, extrasystoles, palpitations

Ear and Labyrinth Disorders: Vertigo, tinnitus, hearing impaired

Gastrointestinal Disorders: Stomatitis, glossitis, esophagitis, gastrooesophageal reflux disease, gastritis, proctalgia, abdominal distension, constipation, dry mouth, eructation, flatulence

General Disorders and Administration Site Conditions: Malaise, pyrexia, asthenia, chest pain, chills, fatigue

Hepatobiliary Disorders: Cholestasis, hepatitis

Immune System Disorders: Hypersensitivity

Infections and Infestations: Cellulitis, gastroenteritis, infection, vaginal infection

Investigations: Blood bilirubin increased, blood alkaline phosphatase increased, blood lactate dehydrogenase increased, albumin globulin ratio abnormal

Metabolism and Nutrition Disorders: Anorexia, decreased appetite

Musculoskeletal and Connective Tissue Disorders: Myalgia, muscle spasms, nuchal rigidity

Nervous System Disorders: Dizziness, tremor, loss of consciousness, dyskinesia, somnolence Psychiatric Disorders: Anxiety, nervousness

Renal and Urinary Disorders: Blood creatinine increased, blood urea increased

Respiratory, Thoracic and Mediastinal Disorders: Asthma, epistaxis, pulmonary embolism

Skin and Subcutaneous Tissue Disorders: Urticaria, dermatitis bullous, pruritus, hyperhidrosis, rash maculo-papular.

All-Cause Mortality in Patients with Coronary Artery Disease 1 to 10 Years Following Clarithromycin Exposure

In one clinical trial evaluating treatment with clarithromycin on outcomes in patients with coronary artery disease, an increase in risk of all-cause mortality was observed in patients randomized to clarithromycin. Clarithromycin for treatment of coronary artery disease is not an approved indication. Patients were treated with clarithromycin or placebo for 14 days and observed for primary outcome events (e.g., all-cause mortality or non-fatal cardiac events) for several years.^1 A numerically higher number of primary outcome events in patients randomized to receive clarithromycin was observed with a hazard ratio of 1.06 (95% confidence interval 0.98 to 1.14). However, at follow-up 10 years post-treatment, there were 866 (40%) deaths in the clarithromycin group and 815 (37%) deaths in the placebo group that represented a hazard ratio for all-cause mortality of 1.10 (95% confidence interval 1.00 to 1.21). The difference in the number of deaths emerged after one year or more after the end of treatment.

The cause of the difference in all-cause mortality has not been established. Other epidemiologic studies evaluating this risk have shown variable results [see Warnings and Precautions (5.5)].

6.2 Postmarketing Experience

The following adverse reactions have been identified during post approval use of clarithromycin. Because these reactions are reported voluntarily from a population of uncertain size, it is not always possible to reliably estimate their frequency or establish a causal relationship to drug exposure.

Blood and Lymphatic System

Thrombocytopenia, agranulocytosis

Cardiac

Ventricular arrhythmia, ventricular tachycardia, torsades de pointes

Ear and Labyrinth

Deafness was reported chiefly in elderly women and was usually reversible.

Gastrointestinal

Pancreatitis acute, tongue discoloration, tooth discoloration was reported and was usually reversible with professional cleaning upon discontinuation of the drug.

Hepatobiliary

Hepatic failure, jaundice hepatocellular. Adverse reactions related to hepatic dysfunction have been reported with clarithromycin [see Warnings and Precautions (5.2)].

Infections and Infestations

Pseudomembranous colitis [see Warnings and Precautions (5.6)]

Immune System

Anaphylactic reactions, angioedema

Investigations

Prothrombin time prolonged, white blood cell count decreased, international normalized ratio increased. Abnormal urine color has been reported, associated with hepatic failure.

Metabolism and Nutrition

Hypoglycemia has been reported in patients taking oral hypoglycemic agents or insulin.

Musculoskeletal and Connective Tissue

Myopathy rhabdomyolysis was reported and in some of the reports, clarithromycin was administered concomitantly with statins, fibrates, colchicine or allopurinol [see Contraindications (4.5) and Warnings and Precautions (5.4)].

Nervous System

Parosmia, anosmia, ageusia, paresthesia and convulsions.

Psychiatric

Abnormal behavior, confusional state, depersonalization, disorientation, hallucination, depression, manic behavior, abnormal dream, psychotic disorder. These disorders usually resolve upon discontinuation of the drug.

Renal and Urinary

Nephritis interstitial, renal failure

Skin and Subcutaneous Tissue

Stevens-Johnson syndrome, toxic epidermal necrolysis, drug rash with eosinophilia and systemic symptoms (DRESS), Henoch-Schonlein purpura, acne, acute generalized exanthematous pustulosis.

Vascular

Hemorrhage

7 DRUG INTERACTIONS

Co-administration of clarithromycin is known to inhibit CYP3A, and a drug primarily metabolized by CYP3A may be associated with elevations in drug concentrations that could increase or prolong both therapeutic and adverse effects of the concomitant drug.

Clarithromycin should be used with caution in patients receiving treatment with other drugs known to be CYP3A enzyme substrates, especially if the CYP3A substrate has a narrow safety margin (e.g., carbamazepine) and/or the substrate is extensively metabolized by this enzyme. Adjust dosage when appropriate and monitor serum concentrations of drugs primarily metabolized by CYP3A closely in patients concurrently receiving clarithromycin.

Table 8: Clinically Significant Drug Interactions with Clarithromycin

Drugs That Are Affected By Clarithromycin
Drug(s) with Pharmacokinetics Affected by Clarithromycin | Recommendation | Comments
Antiarrhythmics
Disopyramide; Quinidine; Dofetilide; Amiodarone; Sotalol; Procainamide | Not; Recommended | Disopyramide, Quinidine: There have been postmarketing reports of torsades de pointes occurring with concurrent use of clarithromycin and quinidine or disopyramide. Electrocardiograms should be monitored for QTc prolongation during coadministration of clarithromycin with these drugs [see Warnings and Precautions (5.2)].; Serum concentrations of these medications should also be monitored. There have been spontaneous or published reports of CYP3A based interactions of clarithromycin with disopyramide and quinidine.; There have been postmarketing reports of hypoglycemia with the concomitant administration of clarithromycin and disopyramide. Therefore, blood glucose levels should be monitored during concomitant administration of clarithromycin and disopyramide.
Digoxin | Use With Caution | Digoxin: Digoxin is a substrate for P-glycoprotein (Pgp) and clarithromycin is known to inhibit Pgp. When clarithromycin and digoxin are co‑ administered, inhibition of Pgp by clarithromycin may lead to increased exposure of digoxin. Elevated digoxin serum concentrations in patients receiving clarithromycin and digoxin concomitantly have been reported in postmarketing surveillance. Some patients have shown clinical signs consistent with digoxin toxicity, including potentially fatal arrhythmias. Monitoring of serum digoxin concentrations should be considered, especially for patients with digoxin concentrations in the upper therapeutic range.
Oral Anticoagulants; Warfarin | Use With Caution | Oral anticoagulants: Spontaneous reports in the postmarketing period suggest that concomitant administration of clarithromycin and oral anticoagulants may potentiate the effects of the oral anticoagulants. Prothrombin times should be carefully monitored while patients are receiving clarithromycin and oral anticoagulants simultaneously [see Warnings and Precautions (5.4)].
Antiepileptics
Carbamazepine | Use With Caution | Carbamazepine: Concomitant administration of single doses of clarithromycin and carbamazepine has been shown to result in increased plasma concentrations of carbamazepine. Blood level monitoring of carbamazepine may be considered. Increased serum concentrations of carbamazepine were observed in clinical trials with clarithromycin. There have been spontaneous or published reports of CYP3A based interactions of clarithromycin with carbamazepine.
Antifungals; Itraconazole | Use With Caution | Itraconazole: Both clarithromycin and itraconazole are substrates and inhibitors of CYP3A, potentially leading to a bi-directional drug interaction when administered concomitantly (see also Itraconazole under “Drugs That Affect Clarithromycin” in the table below). Clarithromycin may increase the plasma concentrations of itraconazole. Patients taking itraconazole and clarithromycin concomitantly should be monitored closely for signs or symptoms of increased or prolonged adverse reactions.
Fluconazole | No Dose Adjustment | Fluconazole: [see Pharmacokinetics (12.3)]
Anti-Gout Agents
Colchicine (in patients; with renal or hepatic; impairment) | Contraindicated | Colchicine: Colchicine is a substrate for both CYP3A and the efflux transporter, P-glycoprotein (Pgp). Clarithromycin and other macrolides are known to inhibit CYP3A and Pgp.
Colchicine (in patients; with normal renal and; hepatic function) | Use With Caution | The dose of colchicine should be reduced when co-administered with clarithromycin in patients with normal renal and hepatic function [see Contraindications (4.4) and Warnings and Precautions (5.4)].
Antipsychotics
Pimozide; Quetiapine; Lurasidone | Contraindicated | Pimozide: [see Contraindications (4.2)]; Quetiapine: Quetiapine is a substrate for CYP3A4, which is inhibited by clarithromycin. Co‑ administration with clarithromycin could result in increased quetiapine exposure and possible quetiapine related toxicities. There have been postmarketing reports of somnolence, orthostatic hypotension, altered state of consciousness, neuroleptic malignant syndrome, and QT prolongation during concomitant administration. Refer to quetiapine prescribing information for recommendations on dose reduction if co‑ administered with CYP3A4 inhibitors such as clarithromycin.; Lurasidone: [See Contraindications (4.7)]
Antispasmodics:; Tolterodine; (patients deficient in CYP2D6 activity) | Use With Caution | Tolterodine: The primary route of metabolism for tolterodine is via CYP2D6. However, in a subset of the population devoid of CYP2D6, the identified pathway of metabolism is via CYP3A. In this population subset, inhibition of CYP3A results in significantly higher serum concentrations of tolterodine. Tolterodine 1 mg twice daily is recommended in patients deficient in CYP2D6 activity (poor metabolizers) when co-administered with clarithromycin.
Antivirals
Atazanavir | Use With Caution | Atazanavir: Both clarithromycin and atazanavir are substrates and inhibitors of CYP3A, and there is evidence of a bi-directional drug interaction (see Atazanavir under “Drugs That Affect Clarithromycin” in the table below) [see Pharmacokinetics (12.3)].
Saquinavir (in patients with decreased renal function) |  | Saquinavir: Both clarithromycin and saquinavir are substrates and inhibitors of CYP3A and there is evidence of a bi-directional drug interaction (see Saquinavir under “Drugs That Affect Clarithromycin” in the table below) [see Pharmacokinetics (12.3)].
Ritonavir, Etravirine |  | Ritonavir, Etravirine: (see Ritonavir and Etravirine under “Drugs That Affect Clarithromycin” in the table below) [see Pharmacokinetics (12.3)].
Maraviroc |  | Maraviroc: Clarithromycin may result in increases in maraviroc exposures by inhibition of CYP3A metabolism. See Selzentry® prescribing information for dose recommendation when given with strong CYP3A inhibitors such as clarithromycin.
Boceprevir (in patients with normal renal function); Didanosine | No Dose; Adjustment | Boceprevir: Both clarithromycin and boceprevir are substrates and inhibitors of CYP3A, potentially leading to a bi-directional drug interaction when co‑ administered. No dose adjustments are necessary for patients with normal renal function (see Victrelis® prescribing information).
Zidovudine |  | Zidovudine: Simultaneous oral administration of clarithromycin immediate-release tablets and zidovudine to HIV-infected adult patients may result in decreased steady-state zidovudine concentrations. Administration of clarithromycin and zidovudine should be separated by at least two hours [see Pharmacokinetics (12.3)].; The impact of co-administration of clarithromycin extended-release tablets or granules and zidovudine has not been evaluated.
Calcium Channel; Blockers
Verapamil | Use With Caution | Verapamil: Hypotension, bradyarrhythmias, and lactic acidosis have been observed in patients receiving concurrent verapamil [see Warnings and Precautions (5.4)].
Amlodipine, Diltiazem |  | Amlodipine, Diltiazem: [see Warnings and Precautions (5.4)]
Nifedipine |  | Nifedipine: Nifedipine is a substrate for CYP3A. Clarithromycin and other macrolides are known to inhibit CYP3A. There is potential of CYP3A‑ mediated interaction between nifedipine and clarithromycin. Hypotension and peripheral edema were observed when clarithromycin was taken concomitantly with nifedipine [see Warnings and Precautions (5.4)].
Ergot Alkaloids
Ergotamine; Dihydroergotamine | Contraindicated | Ergotamine, Dihydroergotamine: Postmarketing reports indicate that coadministration of clarithromycin with ergotamine or dihydroergotamine has been associated with acute ergot toxicity characterized by vasospasm and ischemia of the extremities and other tissues including the central nervous system [see Contraindications (4.6)].
Gastroprokinetic Agents
Cisapride | Contraindicated | Cisapride: [see Contraindications (4.2)]
Lipid-lowering Agents
Lomitapide; Lovastatin; Simvastatin | Contraindicated | Lomitapide, Lovastatin, Simvastatin: Clarithromycin may increase the exposure of these drugs by inhibition of CYP3A metabolism, thereby increasing the risk of toxicities from these drugs [see Contraindications (4.5) and Warnings and Precautions (5.4)]; Atorvastatin, Pravastatin, Fluvastatin: [see Warnings and Precautions (5.4)]
Atorvastatin; Pravastatin | Use With Caution | Lomitapide, Lovastatin, Simvastatin: Clarithromycin may increase the exposure of these drugs by inhibition of CYP3A metabolism, thereby increasing the risk of toxicities from these drugs [see Contraindications (4.5) and Warnings and Precautions (5.4)]; Atorvastatin, Pravastatin, Fluvastatin: [see Warnings and Precautions (5.4)]
Fluvastatin | No Dose; Adjustment | Lomitapide, Lovastatin, Simvastatin: Clarithromycin may increase the exposure of these drugs by inhibition of CYP3A metabolism, thereby increasing the risk of toxicities from these drugs [see Contraindications (4.5) and Warnings and Precautions (5.4)]; Atorvastatin, Pravastatin, Fluvastatin: [see Warnings and Precautions (5.4)]
Hypoglycemic Agents
Nateglinide Pioglitazone Repaglinide Rosiglitazone | Use With Caution | Nateglinide, Pioglitazone, Repaglinide, Rosiglitazone: [see Warnings and Precautions (5.4) and Adverse Reactions (6.2)]
Insulin |  | Insulin: [see Warnings and Precautions (5.4) and Adverse Reactions (6.2)]
Immunosuppressants
Cyclosporine | Use With Caution | Cyclosporine: There have been spontaneous or published reports of CYP3A based interactions of clarithromycin with cyclosporine.
Tacrolimus |  | Tacrolimus: There have been spontaneous or published reports of CYP3A based interactions of clarithromycin with tacrolimus.
Phosphodiesterase inhibitors
Sildenafil; Tadalafil; Vardenafil | Use With Caution | Sildenafil, Tadalafil, Vardenafil: Each of these phosphodiesterase inhibitors is primarily metabolized by CYP3A, and CYP3A will be inhibited by concomitant administration of clarithromycin. Co-administration of clarithromycin with sildenafil, tadalafil, or vardenafil will result in increased exposure of these phosphodiesterase inhibitors. Co-administration of these phosphodiesterase inhibitors with clarithromycin is not recommended. Increased systemic exposure of these drugs may occur with clarithromycin; reduction of dosage for phosphodiesterase inhibitors should be considered (see their respective prescribing information).
Proton Pump Inhibitors
Omeprazole | No Dose; Adjustment | Omeprazole: The mean 24-hour gastric pH value was 5.2 when omeprazole was administered alone and 5.7 when coadministered with clarithromycin as a result of increased omeprazole exposures [see Pharmacokinetics (12.3)] (see also Omeprazole under “Drugs That Affect Clarithromycin” in the table below).
Xanthine Derivatives
Theophylline | Use With Caution | Theophylline: Clarithromycin use in patients who are receiving theophylline may be associated with an increase of serum theophylline concentrations [see Pharmacokinetics (12.3)]. Monitoring of serum theophylline concentrations should be considered for patients receiving high doses of theophylline or with baseline concentrations in the upper therapeutic range.
Triazolobenzodiazepines and Other Related Benzodiazepines
Midazolam | Use With Caution | Midazolam: When oral midazolam is co‑ administered with clarithromycin, dose adjustments may be necessary and possible prolongation and intensity of effect should be anticipated [see Warnings and Precautions (5.4) and Pharmacokinetics (12.3)].
Alprazolam; Triazolam |  | Triazolam, Alprazolam: Caution and appropriate dose adjustments should be considered when triazolam or alprazolam is co-administered with clarithromycin. There have been postmarketing reports of drug interactions and central nervous system (CNS) effects (e.g., somnolence and confusion) with the concomitant use of clarithromycin and triazolam. Monitoring the patient for increased CNS pharmacological effects is suggested.; In postmarketing experience, erythromycin has been reported to decrease the clearance of triazolam and midazolam, and thus, may increase the pharmacologic effect of these benzodiazepines.
Temazepam; Nitrazepam; Lorazepam | No Dose; Adjustment | Temazepam, Nitrazepam, Lorazepam: For benzodiazepines which are not metabolized by CYP3A (e.g., temazepam, nitrazepam, lorazepam), a clinically important interaction with clarithromycin is unlikely.
Cytochrome P450 Inducers
Rifabutin | Use With Caution | Rifabutin: Concomitant administration of rifabutin and clarithromycin resulted in an increase in rifabutin, and decrease in clarithromycin serum levels together with an increased risk of uveitis (see Rifabutin under “Drugs That Affect Clarithromycin” in the table below).
Other Drugs Metabolized by CYP3A
Alfentanil; Bromocriptine; Cilostazol; Vinblastine; Methylprednisolone; Phenobarbital; St. John’s Wort | Use With Caution | There have been spontaneous or published reports of CYP3A based interactions of clarithromycin with alfentanil, methylprednisolone, cilostazol, bromocriptine, vinblastine, phenobarbital, and St. John’s Wort.
Other Drugs Metabolized by CYP450 Isoforms Other than CYP3A
Hexobarbital; Phenytoin; Valproate | Use With Caution | There have been postmarketing reports of interactions of clarithromycin with drugs not thought to be metabolized by CYP3A, including hexobarbital, phenytoin, and valproate.
Drugs that Affect Clarithromycin
Drug(s) that Affect the Pharmacokinetics of Clarithromycin | Recommendation | Comments
Antifungals
Itraconazole | Use With Caution | Itraconazole: Itraconazole may increase the plasma concentrations of clarithromycin. Patients taking itraconazole and clarithromycin concomitantly should be monitored closely for signs or symptoms of increased or prolonged adverse reactions (see also Itraconazole under “Drugs That Are Affected By Clarithromycin” in the table above).
Antivirals
Atazanavir | Use With Caution | Atazanavir: When clarithromycin is co-administered with atazanavir, the dose of clarithromycin should be decreased by 50% [see Clinical Pharmacology (12.3)].; Since concentrations of 14-OH clarithromycin are significantly reduced when clarithromycin is co‑ administered with atazanavir, alternative antibacterial therapy should be considered for indications other than infections due to Mycobacterium avium complex. Doses of clarithromycin greater than 1000 mg per day should not be co-administered with protease inhibitors.
Ritonavir (in patients with decreased renal function) |  | Ritonavir: Since concentrations of 14-OH clarithromycin are significantly reduced when clarithromycin is co-administered with ritonavir, alternative antibacterial therapy should be considered for indications other than infections due to Mycobacterium avium [see Pharmacokinetics (12.3)]. Doses of clarithromycin greater than 1000 mg per day should not be co-administered with protease inhibitors.
Saquinavir (in patients with decreased renal function) |  | Saquinavir: When saquinavir is co-administered with ritonavir, consideration should be given to the potential effects of ritonavir on clarithromycin (refer to ritonavir above) [see Pharmacokinetics (12.3)].
Etravirine |  | Etravirine: Clarithromycin exposure was decreased by etravirine; however, concentrations of the active metabolite, 14-OH-clarithromycin, were increased. Because 14-OH-clarithromycin has reduced activity against Mycobacterium avium complex (MAC), overall activity against this pathogen may be altered; therefore alternatives to clarithromycin should be considered for the treatment of MAC.
Saquinavir (in patients with normal renal function); Ritonavir (in patients with normal renal function) | No Dose Adjustment
Proton Pump Inhibitors
Omeprazole | Use With Caution | Omeprazole: Clarithromycin concentrations in the gastric tissue and mucus were also increased by concomitant administration of omeprazole [see Pharmacokinetics (12.3)].
Miscellaneous Cytochrome P450 Inducers
Efavirenz; Nevirapine; Rifampicin; Rifabutin; Rifapentine | Use With Caution | Inducers of CYP3A enzymes, such as efavirenz, nevirapine, rifampicin, rifabutin, and rifapentine will increase the metabolism of clarithromycin, thus decreasing plasma concentrations of clarithromycin, while increasing those of 14-OH-clarithromycin. Since the microbiological activities of clarithromycin and 14-OH-clarithromycin are different for different bacteria, the intended therapeutic effect could be impaired during concomitant administration of clarithromycin and enzyme inducers. Alternative antibacterial treatment should be considered when treating patients receiving inducers of CYP3A. There have been spontaneous or published reports of CYP3A based interactions of clarithromycin with rifabutin (see Rifabutin under “Drugs That Are Affected By Clarithromycin” in the table above).

8 USE IN SPECIFIC POPULATIONS

8.1 Pregnancy

Risk Summary

Based on findings from animal studies, clarithromycin is not recommended for use in pregnant women except in clinical circumstances where no alternative therapy is appropriate. If pregnancy occurs while taking clarithromycin, the patient should be apprised of the potential hazard to the fetus [see Warnings and Precautions (5.7)].

Limited data from a small number of published human studies with clarithromycin use during pregnancy are insufficient to inform drug-associated risks of major birth defects, miscarriage, or adverse maternal or fetal outcomes. In animal reproduction studies, administration of oral clarithromycin to pregnant mice, rats, rabbits, and monkeys during the period of organogenesis produced malformations in rats (cardiovascular anomalies) and mice (cleft palate) at clinically relevant doses based on body surface area comparison. Fetal effects in mice, rats, and monkeys (e.g., reduced fetal survival, body weight, body weight gain) and implantation losses in rabbits were generally considered to be secondary to maternal toxicity (see Data).

The estimated background risk of major birth defects and miscarriage for the indicated population is unknown. All pregnancies have a background risk of birth defect, loss, or other adverse outcomes. In the U.S. general population, the estimated background risk of major birth defects and miscarriage in clinically recognized pregnancies is 2% to 4% and 15% to 20%, respectively.

Data

Animal Data

Animal reproduction studies were conducted in mice, rats, rabbits, and monkeys with oral and intravenously administered clarithromycin. In pregnant mice, clarithromycin was administered during organogenesis (gestation day [GD] 6 to 15) at oral doses of 15, 60, 250, 500, or 1000 mg/kg/day. Reduced body weight observed in dams at 1000 mg/kg/day (3 times the maximum recommended human dose [MRHD] based on body surface area comparison) resulted in reduced survival and body weight of the fetuses. At ≥500 mg/kg/day, increases in the incidence of post-implantation loss and cleft palate in the fetuses were observed. No adverse developmental effects were observed in mice at ≤250 mg/kg/day (≤1 times MRHD based on body surface area comparison).

In pregnant Sprague Dawley rats, clarithromycin was administered during organogenesis (GD 6 to 15) at oral doses of 15, 50, or 150 mg/kg/day. Reductions in body weight and food consumption was observed in dams at 150 mg/kg/day. Increased resorptions and reduced body weight of the fetuses at this dose were considered secondary to maternal toxicity. Additionally, at 150 mg/kg/day (1 times MRHD based on body surface area comparison), a low incidence of cardiovascular anomalies (complete situs inversus, undivided truncus, IV septal defect) was observed in the fetuses. Clarithromycin did not cause adverse developmental effects in rats at 50 mg/kg/day (0.3 times MRHD based on body surface area comparison). Intravenous dosing of clarithromycin during organogenesis in rats (GD 6 to 15) at 15, 50, or 160 mg/kg/day was associated with maternal toxicity (reduced body weight, body-weight gain, and food consumption) at 160 mg/kg/day but no evidence of adverse developmental effects at any dose (≤1 times MRHD based on body surface area comparison).

In pregnant Wistar rat, clarithromycin was administered during organogenesis (GD 7 to 17) at oral doses of 10, 40, or 160 mg/kg/day. Reduced body weight and food consumption were observed in dams at 160 mg/kg/day but there was no evidence of adverse developmental effects at any dose (≤1 times MRHD based on body surface area comparison).

In pregnant rabbits, clarithromycin administered during organogenesis (GD 6 to 18) at oral doses of 10, 35, or 125 mg/kg/day resulted in reduced maternal food consumption and decreased body weight at the highest dose, with no evidence of any adverse developmental effects at any dose (≤ 2 times MRHD based on body surface area comparison). Intravenously administered clarithromycin to pregnant rabbits during organogenesis (GD 6 to 18) in rabbits at 20, 40, 80, or 160 mg/kg/day (≥0.3 times MRHD based on body surface area comparison) resulted in maternal toxicity and implantation losses at all doses.

In pregnant monkeys, clarithromycin was administered (GD 20 to 50) at oral doses of 35 or 70 mg/kg/day. Dose-dependent emesis, poor appetite, fecal changes, and reduced body weight were observed in dams at all doses (≥0.5 times MRHD based on body surface area comparison). Growth retardation in 1 fetus at 70 mg/kg/day was considered secondary to maternal toxicity. There was no evidence of primary drug related adverse developmental effects at any dose tested.

In a reproductive toxicology study in rats administered oral clarithromycin late in gestation through lactation (GD 17 to post-natal day 21) at doses of 10, 40, or 160 mg/kg/day (≤1 times MRHD based on body surface area comparison), reductions in maternal body weight and food consumption were observed at 160 mg/kg/day. Reduced body-weight gain observed in offspring at 160 mg/kg/day was considered secondary to maternal toxicity. No adverse developmental effects were observed with clarithromycin at any dose tested.

8.2 Lactation

Risk Summary

Based on limited human data, clarithromycin and its active metabolite 14-OH clarithromycin are present in human milk at less than 2% of the maternal weight-adjusted dose (see Data). In a separate observational study, reported adverse effects on breast-fed children (rash, diarrhea, loss of appetite, somnolence) were comparable to amoxicillin (see Data). No data are available to assess the effects of clarithromycin or 14-OH clarithromycin on milk production.

The development and health benefits of breastfeeding should be considered along with the mother’s clinical need for clarithromycin and any potential adverse effects on the breast-fed child from clarithromycin or from the underlying maternal condition.

Data

Human

Serum and milk samples were obtained after 3 days of treatment, at steady state, from one published study of 12 lactating women who were taking clarithromycin 250 mg orally twice daily. Based on the limited data from this study, and assuming milk consumption of 150 mL/kg/day, an exclusively human milk fed infant would receive an estimated average of 136 mcg/kg/day of clarithromycin and its active metabolite, with this maternal dosage regimen. This is less than 2% of the maternal weight-adjusted dose (7.8 mg/kg/day, based on the average maternal weight of 64 kg), and less than 1% of the pediatric dose (15 mg/kg/day) for children greater than 6 months of age.

A prospective observational study of 55 breastfed infants of mothers taking a macrolide antibacterial (6 were exposed to clarithromycin) were compared to 36 breastfed infants of mothers taking amoxicillin. Adverse reactions were comparable in both groups. Adverse reactions occurred in 12.7% of infants exposed to macrolides and included rash, diarrhea, loss of appetite, and somnolence.

8.3 Females and Males of Reproductive Potential

Males

Administration of clarithromycin resulted in testicular atrophy in rats, dogs and monkeys [see Nonclinical Toxicology (13.1)].

8.4 Pediatric Use

The safety and effectiveness of clarithromycin for oral suspension have been established for the treatment of the following conditions or diseases in pediatric patients 6 months and older. Use in these indications is based on clinical trials in pediatric patients or adequate and well- controlled studies in adults with additional pharmacokinetic and safety data in pediatric patients:

• Pharyngitis/Tonsillitis

• Community-Acquired Pneumonia

• Acute maxillary sinusitis

• Acute otitis media [see Clinical Studies (14.2)]

• Uncomplicated skin and skin structure infections

The safety and effectiveness of clarithromycin for oral suspension have been established for the prevention of disseminated Mycobacterium avium complex (MAC) disease in pediatric patients 20 months and older with advanced HIV infection. No studies of clarithromycin for MAC prophylaxis have been performed in pediatric populations and the doses recommended for prophylaxis are derived from MAC pediatric treatment studies.

Safety and effectiveness of clarithromycin in pediatric patients under 6 months of age have not been established. The safety of clarithromycin has not been studied in MAC patients under the age of 20 months.

8.5 Geriatric Use

In a steady-state study in which healthy elderly subjects (65 years to 81 years of age) were given 500 mg of clarithromycin every 12 hours, the maximum serum concentrations and area under the curves of clarithromycin and 14-OH clarithromycin were increased compared to those achieved in healthy young adults. These changes in pharmacokinetics parallel known age-related decreases in renal function. In clinical trials, elderly patients did not have an increased incidence of adverse reactions when compared to younger patients. Consider dosage adjustment in elderly patients with severe renal impairment. Elderly patients may be more susceptible to development of torsades de pointes arrhythmias than younger patients [see Warnings and Precautions (5.3)].

Most reports of acute kidney injury with calcium channel blockers metabolized by CYP3A4 (e.g., verapamil, amlodipine, diltiazem, nifedipine) involved elderly patients 65 years of age or older [see Warnings and Precautions (5.4)].

Especially in elderly patients, there have been reports of colchicine toxicity with concomitant use of clarithromycin and colchicine, some of which occurred in patients with renal insufficiency. Deaths have been reported in some patients [see Contraindications (4.4) and Warnings and Precautions (5.4)].

8.6 Renal and Hepatic Impairment

Clarithromycin is principally excreted via the liver and kidney. Clarithromycin may be administered without dosage adjustment to patients with hepatic impairment and normal renal function. However, in the presence of severe renal impairment with or without coexisting hepatic impairment, decreased dosage or prolonged dosing intervals may be appropriate [see Dosage and Administration (2.5)].

10 OVERDOSAGE

Overdosage of clarithromycin can cause gastrointestinal symptoms such as abdominal pain, vomiting, nausea, and diarrhea.

Treat adverse reactions accompanying overdosage by the prompt elimination of unabsorbed drug and supportive measures. As with other macrolides, clarithromycin serum concentrations are not expected to be appreciably affected by hemodialysis or peritoneal dialysis.

11 DESCRIPTION

Clarithromycin is a semi-synthetic macrolide antimicrobial for oral use. Chemically, it is
6-0‑ methylerythromycin. The molecular formula is C38H69NO13, and the molecular weight is 747.96. The structural formula is:

Figure 1: Structure of Clarithromycin

Clarithromycin is a white to off-white crystalline powder. It is soluble in acetone, slightly soluble in methanol, ethanol, and acetonitrile, and practically insoluble in water.

Clarithromycin is available as granules for oral suspension.

After constitution, each 5 mL of clarithromycin for oral suspension, USP contains 125 mg or 250 mg of clarithromycin. Each bottle of clarithromycin granules for oral suspension contains 1250 mg (50 mL size), 2500 mg (50 and 100 mL sizes) or 5000 mg (100 mL size) of clarithromycin and the following inactive ingredients: citric acid (anhydrous), colloidal silicon dioxide, confectioner’s sugar, fruit punch flavor, glyceryl monostearate, hypromellose, maltodextrin, methacrylic acid copolymer dispersion, poloxamer, polyethylene glycol, polysorbate 80, potassium sorbate, povidone, titanium dioxide, triethyl citrate, and xanthan gum.

12 CLINICAL PHARMACOLOGY

12.1 Mechanism of Action

Clarithromycin is a macrolide antimicrobial drug [see Microbiology (12.4)].

12.3 Pharmacokinetics

Absorption

Clarithromycin Granules For Oral Suspension

When 250 mg doses of clarithromycin for oral suspension were administered to fasting healthy adult subjects, peak plasma concentrations were attained around 3 hours after dosing.

For adult patients, the bioavailability of 10 mL of the 125 mg/5 mL suspension or 10 mL of the 250 mg/5 mL suspension is similar to a 250 mg or 500 mg tablet, respectively.

In adults given 250 mg clarithromycin as suspension (n = 22), food appeared to decrease mean peak plasma clarithromycin concentrations from 1.2 (± 0.4) mcg/mL to 1.0 (± 0.4) mcg/mL and the extent of absorption from 7.2 (± 2.5) hr•mcg/mL to 6.5 (± 3.7) hr•mcg/mL.

Distribution

Clarithromycin and the 14-OH clarithromycin metabolite distribute readily into body tissues and fluids. There are no data available on cerebrospinal fluid penetration. Because of high intracellular concentrations, tissue concentrations are higher than serum concentrations. Examples of tissue and serum concentrations are presented below.

Table 9. Tissue and Serum Concentrations of Clarithromycin

CONCENTRATION (after 250 mg every 12 hours)
Tissue Type | Tissue(mcg/g) | Serum(mcg/mL)
Tonsil | 1.6 | 0.8
Lung | 8.8 | 1.7

Specific Populations for Clarithromycin Granules Formulations

Clarithromycin Granules For Oral Suspension in Pediatric Patients

Clarithromycin penetrates into the middle ear fluid of pediatric patients with secretory otitis media.

Table 10. Middle Ear Fluid and Serum Concentrations of Clarithromycin and 14-OH-Clarithromycin in Pediatric Patients

CONCENTRATION (after 7.5 mg/kg every 12 hours for 5 doses)
Analyte | Middle Ear Fluid (mcg/mL) | Serum (mcg/mL)
Clarithromycin | 2.5 | 1.7
14-OH Clarithromycin | 1.3 | 0.8

When pediatric patients (n = 10) were administered a single oral dose of 7.5 mg/kg clarithromycin as an oral suspension, food increased mean peak plasma clarithromycin concentrations from 3.6 (± 1.5) mcg/mL to 4.6 (± 2.8) mcg/mL and the extent of absorption from 10.0 (± 5.5) hr•mcg/mL to 14.2 (± 9.4) hr•mcg/mL.

In pediatric patients requiring antibacterial therapy, administration of 7.5 mg/kg every 12 hours of clarithromycin as an oral suspension generally resulted in steady-state peak plasma concentrations of 3 mcg/mL to 7 mcg/mL for clarithromycin and 1 mcg/mL to 2 mcg/mL for 14-OH clarithromycin.

In HIV-infected pediatric patients taking 15 mg/kg of clarithromycin as an oral suspension every 12 hours, steady-state clarithromycin peak concentrations generally ranged from 6 mcg/mL to 15 mcg/mL.

HIV Infection

Steady-state concentrations of clarithromycin and 14-OH clarithromycin observed following administration of 500 mg doses of clarithromycin every 12 hours to adult patients with HIV infection were similar to those observed in healthy volunteers. In adult HIV-infected patients taking 500-mg or 1000-mg doses of clarithromycin every 12 hours, steady-state clarithromycin Cmax values ranged from 2 mcg/mL to 4 mcg/mL and 5 mcg/mL to 10 mcg/mL, respectively.

Hepatic Impairment

The steady-state concentrations of clarithromycin in subjects with impaired hepatic function did not differ from those in normal subjects; however, the 14-OH clarithromycin concentrations were lower in the hepatically impaired subjects. The decreased formation of 14-OH clarithromycin was at least partially offset by an increase in renal clearance of clarithromycin in the subjects with impaired hepatic function when compared to healthy subjects.

Renal Impairment

The pharmacokinetics of clarithromycin was also altered in subjects with impaired renal function

[see Use in Specific Populations (8.6) and Dosage and Administration (2.5)].

Drug Interactions

Fluconazole

Following administration of fluconazole 200 mg daily and clarithromycin 500 mg twice daily to 21 healthy volunteers, the steady-state clarithromycin Cmin and AUC increased 33% and 18%, respectively. Clarithromycin exposures were increased and steady-state concentrations of 14-OH clarithromycin were not significantly affected by concomitant administration of fluconazole.

Colchicine

When a single dose of colchicine 0.6 mg was administered with clarithromycin
250 mg BID for 7 days, the colchicine Cmax increased 197% and the AUC0-∞ increased 239% compared to administration of colchicine alone.

Atazanavir

Following administration of clarithromycin (500 mg twice daily) with atazanavir (400 mg once daily), the clarithromycin AUC increased 94%, the 14-OH clarithromycin AUC decreased 70% and the atazanavir AUC increased 28%.

Ritonavir

Concomitant administration of clarithromycin and ritonavir (n = 22) resulted in a 77% increase in clarithromycin AUC and a 100% decrease in the AUC of 14-OH clarithromycin.

Saquinavir

Following administration of clarithromycin (500 mg bid) and saquinavir (soft gelatin capsules, 1200 mg tid) to 12 healthy volunteers, the steady-state saquinavir AUC and Cmax increased 177% and 187% respectively compared to administration of saquinavir alone. Clarithromycin AUC and Cmax increased 45% and 39% respectively, whereas the 14–OH clarithromycin AUC and Cmax decreased 24% and 34% respectively, compared to administration with clarithromycin alone.

Didanosine

Simultaneous administration of clarithromycin tablets and didanosine to 12 HIV-infected adult patients resulted in no statistically significant change in didanosine pharmacokinetics.

Zidovudine

Following administration of clarithromycin 500 mg tablets twice daily with zidovudine 100 mg every 4 hours, the steady-state zidovudine AUC decreased 12% compared to administration of zidovudine alone (n=4). Individual values ranged from a decrease of 34% to an increase of 14%. When clarithromycin tablets were administered two to four hours prior to zidovudine, the steady- state zidovudine Cmax increased 100% whereas the AUC was unaffected (n=24).

Omeprazole

Clarithromycin 500 mg every 8 hours was given in combination with omeprazole 40 mg daily to healthy adult subjects. The steady-state plasma concentrations of omeprazole were increased (Cmax, AUC0-24, and t½ increases of 30%, 89%, and 34%, respectively), by the concomitant administration of clarithromycin.

The plasma levels of clarithromycin and 14–OH clarithromycin were increased by the concomitant administration of omeprazole. For clarithromycin, the mean Cmax was 10% greater, the mean Cmin was 27% greater, and the mean AUC0-8 was 15% greater when clarithromycin was administered with omeprazole than when clarithromycin was administered alone. Similar results were seen for 14–OH clarithromycin, the mean Cmax was 45% greater, the mean Cmin was 57% greater, and the mean AUC0-8 was 45% greater. Clarithromycin concentrations in the gastric tissue and mucus were also increased by concomitant administration of omeprazole.

Clarithromycin Tissue Concentrations 2 hours after Dose (mcg/mL)/(mcg/g)
Treatment | N | antrum | fundus | N | Mucus
Clarithromycin | 5 | 10.48 ± 2.01 | 20.81 ± 7.64 | 4 | 4.15 ± 7.74
Clarithromycin + Omeprazole | 5 | 19.96 ± 4.71 | 24.25 ± 6.37 | 4 | 39.29 ± 32.79

Theophylline

In two studies in which theophylline was administered with clarithromycin (a theophylline sustained-release formulation was dosed at either 6.5 mg/kg or 12 mg/kg together with 250 or 500 mg q12h clarithromycin), the steady-state levels of Cmax, Cmin, and the area under the serum concentration time curve (AUC) of theophylline increased about 20%.

Midazolam

When a single dose of midazolam was co-administered with clarithromycin tablets (500 mg twice daily for 7 days), midazolam AUC increased 174% after intravenous administration of midazolam and 600% after oral administration.

For information about other drugs indicated in combination with clarithromycin, refer to their full prescribing information, CLINICAL PHARMACOLOGY section.

12.4 Microbiology

Mechanism of Action

Clarithromycin exerts its antibacterial action by binding to the 50S ribosomal subunit of susceptible bacteria resulting in inhibition of protein synthesis.

Resistance

The major routes of resistance are modification of the 23S rRNA in the 50S ribosomal subunit to insensitivity or drug efflux pumps. Beta-lactamase production should have no effect on clarithromycin activity.

Most isolates of methicillin-resistant and oxacillin-resistant staphylococci are resistant to clarithromycin.

If H. pylori is not eradicated after treatment with clarithromycin-containing combination regimens, patients may develop clarithromycin resistance in H. pylori isolates. Therefore, for patients who fail therapy, clarithromycin susceptibility testing should be done, if possible. Patients with clarithromycin-resistant H. pylori should not be treated with any of the following: omeprazole/clarithromycin dual therapy; omeprazole/clarithromycin/amoxicillin triple therapy; lansoprazole/clarithromycin/amoxicillin triple therapy; or other regimens which include clarithromycin as the sole antibacterial agent.

Antimicrobial Activity

Clarithromycin has been shown to be active against most of the isolates of the following microorganisms both in vitro and in clinical infections [see Indications and Usage (1)].

Gram-Positive Bacteria

• Staphylococcus aureus

• Streptococcus pneumoniae

• Streptococcus pyogenes

Gram-Negative Bacteria

• Haemophilus influenzae

• Haemophilus parainfluenzae

• Moraxella catarrhalis

Other Microorganisms

• Chlamydophila pneumoniae

• Helicobacter pylori

• Mycobacterium avium complex (MAC) consisting of M. avium and M. intracellulare

• Mycoplasma pneumoniae

At least 90 percent of the microorganisms listed below exhibit in vitro minimum inhibitory concentrations (MICs) less than or equal to the clarithromycin susceptible MIC breakpoint for organisms of similar type to those shown in Table 11. However, the efficacy of clarithromycin in treating clinical infections due to these microorganisms has not been established in adequate and well-controlled clinical trials.

Gram-Positive Bacteria

• Streptococcus agalactiae

• Streptococci (Groups C, F, G)

• Viridans group streptococci

Gram-Negative Bacteria

• Legionella pneumophila

• Pasteurella multocida

Anaerobic Bacteria

• Clostridium perfringens

• Peptococcus niger

• Prevotella melaninogenica

• Propionibacterium acnes

Susceptibility Testing

For specific information regarding susceptibility test interpretive criteria, and associated test methods and quality control standards recognized by FDA for this drug, please see: http://www.fda.gov/STIC.

13 NONCLINICAL TOXICOLOGY

13.1 Carcinogenesis, Mutagenesis, Impairment of Fertility

Mutagenesis

The following in vitro mutagenicity tests have been conducted with clarithromycin:

- Salmonella/Mammalian Microsomes Test
- Bacterial Induced Mutation Frequency Test
- In Vitro Chromosome Aberration Test
- Rat Hepatocyte DNA Synthesis Assay
- Mouse Lymphoma Assay
- Mouse Dominant Lethal Study
- Mouse Micronucleus Test

All tests had negative results except the in vitro chromosome aberration test which was positive in one test and negative in another. In addition, a bacterial reverse-mutation test (Ames test) has been performed on clarithromycin metabolites with negative results.

Impairment of Fertility

Fertility and reproduction studies have shown that daily doses of up to 160 mg/kg/day to male and female rats caused no adverse effects on the estrous cycle, fertility, parturition, or number and viability of offspring. Plasma levels in rats after 150 mg/kg/day were twice the human serum levels.

Testicular atrophy occurred in rats at doses 7 times, in dogs at doses 3 times, and in monkeys at doses 8 times greater than the maximum human daily dose (on a body surface area basis).

13.2 Animal Toxicology and/or Pharmacology

Corneal opacity occurred in dogs at doses 12 times and in monkeys at doses 8 times greater than the maximum human daily dose (on a body surface area basis). Lymphoid depletion occurred in dogs at doses 3 times greater than and in monkeys at doses 2 times greater than the maximum human daily dose (on a body surface area basis).

14 CLINICAL STUDIES

14.1 Mycobacterial Infections

Prophylaxis of Mycobacterial Infections

A randomized, double-blind clinical trial (trial 3) compared clarithromycin 500 mg twice a day to placebo in patients with CDC-defined AIDS and CD4 counts less than 100 cells/µL. This trial accrued 682 patients from November 1992 to January 1994, with a median CD4 cell count at entry of 30 cells/mcL. Median duration of clarithromycin was 10.6 months vs. 8.2 months for placebo. More patients in the placebo arm than the clarithromycin arm discontinued prematurely from the trial (75.6% and 67.4%, respectively). However, if premature discontinuations due to Mycobacterium avium complex (MAC) or death are excluded, approximately equal percentages of patients on each arm (54.8%) on clarithromycin and 52.5% on placebo) discontinued study drug early for other reasons. The trial was designed to evaluate the following endpoints:

1. MAC bacteremia, defined as at least one positive culture for Mycobacterium avium complex bacteria from blood or another normally sterile site
2. Survival
3. Clinically significant disseminated MAC disease, defined as MAC bacteremia accompanied by signs or symptoms of serious MAC infection, including fever, night sweats, weight loss, anemia, or elevations in liver function tests

MAC Bacteremia

In patients randomized to clarithromycin, the risk of MAC bacteremia was reduced by 69% compared to placebo. The difference between groups was statistically significant (p < 0.001). On an intent- to-treat basis, the one-year cumulative incidence of MAC bacteremia was 5.0% for patients randomized to clarithromycin and 19.4% for patients randomized to placebo. While only 19 of the 341 patients randomized to clarithromycin developed MAC, 11 of these cases were resistant to clarithromycin. The patients with resistant MAC bacteremia had a median baseline CD4 count of 10 cells/mm^3 (range 2 cells/mm^3 to 25 cells/mm^3). Information regarding the clinical course and response to treatment of the patients with resistant MAC bacteremia is limited. The 8 patients who received clarithromycin and developed susceptible MAC bacteremia had a median baseline CD4 count of 25 cells/mm^3 (range 10 cells/mm^3 to 80 cells/mm^3). Comparatively, 53 of the 341 placebo patients developed MAC; none of these isolates were resistant to clarithromycin. The median baseline CD4 count was 15 cells/mm^3 (range 2 cells/mm^3 to 130 cells/mm^3) for placebo patients that developed MAC.

Survival

A statistically significant survival benefit of clarithromycin compared to placebo was observed (see Figure 3 and Table 13). Since the analysis at 18 months includes patients no longer receiving prophylaxis the survival benefit of clarithromycin may be underestimated.

Figure 3. Survival of All Randomized AIDS Patients Over Time in Trial 3

Table 13. Mortality Rates at 18 months in Trial 3

 | Mortality Rates |  | Reduction in Mortality Rates on; clarithromycin
 | Placebo | clarithromycin | Reduction in Mortality Rates on; clarithromycin
6 month | 9.4% | 6.5% | 31%
12 month | 29.7% | 20.5% | 31%
18 month | 46.4% | 37.5% | 20%

Clinically Significant Disseminated MAC Disease

In association with the decreased incidence of MAC bacteremia, patients in the group randomized to clarithromycin showed reductions in the signs and symptoms of disseminated MAC disease, including fever, night sweats, weight loss, and anemia.

Treatment of Mycobacterial Infections

Dose-Ranging Monotherapy Trials in Adult AIDS Patients with MAC

Two randomized clinical trials (Trials 1 and 2) compared different dosages of clarithromycin in patients with CDC-defined AIDS and CD4 counts less than100 cells/mcL. These trials accrued patients from May 1991 to March 1992. Trial 500 was a randomized, double-blind trial; trial 577 was an open-label compassionate use trial. Both trials used 500 mg and 1000 mg twice daily dosing of clarithromycin; trial 1 also had a 2000 mg twice daily clarithromycin group. Trial 1 enrolled

154 adult patients and trial 2 enrolled 469 adult patients. The majority of patients had CD4 cell counts less than 50 cells/mcL at study entry. The trials were designed to evaluate the following end points:

1. Change in MAC bacteremia or blood cultures negative for M. avium.
2. Change in clinical signs and symptoms of MAC infection including one or more of the following: fever, night sweats, weight loss, diarrhea, splenomegaly, and hepatomegaly.

The results for trial 1 are described below. The trial 2 results were similar to the results of trial 1.

MAC Bacteremia

Decreases in MAC bacteremia or negative blood cultures were seen in the majority of patients in all clarithromycin dosage groups. The mean reductions in MAC colony forming units (CFU) from baseline after 4 weeks of therapy in the 1000 mg (n=32) twice daily and 2000 mg (n=26) twice daily regimen was 2.3 Log CFU compared to 1.5 Log CFU in the clarithromycin 500 mg twice daily (n=35) regimen. A separate trial with a four-drug regimen^2 (ciprofloxacin, ethambutol, rifampicin, and clofazimine) had a mean reduction of 1.4 Log CFU.

Clinical outcomes evaluated with the different dosing regimens of clarithromycin monotherapy are shown in Table 14. The 1000 mg and 2000 mg twice daily doses showed significantly better control of bacteremia during the first four weeks of therapy. No significant differences were seen beyond that point. All of the isolates had MIC less than 8 mcg/mL at pre-treatment. Relapse was almost always accompanied by an increase in MIC.

Table 14. Outcome with the Different Dosing Regimens of Clarithromycin

Outcome | Clarithromycin 500 mg twice daily | Clarithromycin 1000 mg twice daily | Clarithromycin 2000 mg twice daily
One or more negative blood cultures at any time during acute therapy | 61% (30/49) | 59% (29/49) | 52% (25/48)
Two or more negative blood cultures during acute therapy sustained through study day 84 | 25% (12/49) | 25% (12/49) | 8% (4/48)
Death or discontinuation by day 84 | 23% (11/49) | 37% (18/49) | 56% (27/48)
Relapse by day 84 | 14% (7/49) | 12% (6/49) | 13% (6/48)
Median time to first negative culture (in days) | 54 | 41 | 29
Median time to first decrease of at least 1 log CFU (in days) | 29 | 16 | 15
Median time to first positive culture or study discontinuation following the first negative culture (in days) | 43 | 59 | 43

Clinically Significant Disseminated MAC Disease

Among patients experiencing night sweats prior to therapy, 84% showed resolution or improvement at some point during the 12 weeks of clarithromycin at 500 mg to 2000 mg twice daily doses. Similarly, 77% of patients reported resolution or improvement in fevers at some point. Response rates for clinical signs of MAC are given in Table 15 below.

The median duration of response, defined as improvement or resolution of clinical signs and symptoms, was 2 weeks to 6 weeks.

Since the trial was not designed to determine the benefit of monotherapy beyond 12 weeks, the duration of response may be underestimated for the 25% to 33% of patients who continued to show clinical response after 12 weeks.

Table 15. Response Rates for Clinical Signs of MAC During 6 Weeks to 12 Weeks of Treatment

Resolution of Fever |  |  | Resolution of Night Sweats
clarithromycin twice daily dose (mg) | % ever; afebrile | % afebrile; 6 weeks or more | clarithromycin twice; daily dose (mg) | % ever; resolving | % resolving; 6 weeks or more
500 | 67% | 23% | 500 | 85% | 42%
1000 | 67% | 12% | 1000 | 70% | 33%
2000 | 62% | 22% | 2000 | 72% | 36%

Weight Gain Greater Than 3% |  |  | Hemoglobin Increase Greater Than 1 gm
clarithromycin twice daily dose (mg) | % ever; gaining | % gaining; 6 weeks or more | clarithromycin twice; daily dose (mg) | % ever; increasing | % increasing; 6 weeks or more
500 | 33% | 14% | 500 | 58% | 26%
1000 | 26% | 17% | 1000 | 37% | 6%
2000 | 26% | 12% | 2000 | 62% | 18%

Survival

Median survival time from trial entry (trial 1) was 249 days at the 500 mg twice daily dose compared to 215 days with the 1000 mg twice daily dose. However, during the first 12 weeks of therapy, there were 2 deaths in 53 patients in the 500 mg twice daily group versus 13 deaths in 51 patients in the 1000 mg twice daily group. The reason for this apparent mortality difference is not known. Survival in the two groups was similar beyond 12 weeks. The median survival times for these dosages were similar to recent historical controls with MAC when treated with combination therapies.^2

Median survival time from entry in trial 2 was 199 days for the 500 mg twice a day dose and 179 days for the 1000 mg twice a day dose. During the first four weeks of therapy, while patients were maintained on their originally assigned dose, there were 11 deaths in 255 patients taking 500 mg twice daily and 18 deaths in 214 patients taking 1000 mg twice daily.

Dosage-Ranging Monotherapy Trials in Pediatric AIDS Patients with MAC

Trial 4 was a pediatric trial of 3.75 mg/kg, 7.5 mg/kg, and 15 mg/kg of clarithromycin twice daily in patients with CDC-defined AIDS and CD4 counts less than 100 cells/mcL. The trial enrolled 25 patients between the ages of 1 to 20. The trial evaluated the same endpoints as in the adult trials 1 and 2. Results with the 7.5 mg/kg twice daily dose in the pediatric trial were comparable to those for the 500 mg twice daily regimen in the adult trials.

Combination Therapy in AIDS Patients with Disseminated MAC

Trial 5 compared the safety and efficacy of clarithromycin in combination with ethambutol versus clarithromycin in combination with ethambutol and clofazimine for the treatment of disseminated MAC (dMAC) infection. This 24-week trial enrolled 106 patients with AIDS and dMAC, with 55 patients randomized to receive clarithromycin and ethambutol, and 51 patients randomized to receive clarithromycin, ethambutol, and clofazime. Baseline characteristics between treatment arms were similar with the exception of median CFU counts being at least 1 log higher in the clarithromycin, ethambutol, and clofazime arm.

Compared to prior experience with clarithromycin monotherapy, the two-drug regimen of clarithromycin and ethambutol extended the time to microbiologic relapse, largely through suppressing the emergence of clarithromycin resistant strains. However, the addition of clofazimine to the regimen added no additional microbiologic or clinical benefit. Tolerability of both multidrug regimens was comparable with the most common adverse events being gastrointestinal in nature. Patients receiving the clofazimine-containing regimen had reduced survival rates; however, their baseline mycobacterial colony counts were higher. The results of this trial support the addition of ethambutol to clarithromycin for the treatment of initial dMAC infections but do not support adding clofazimine as a third agent.

14.2 Otitis Media

Otitis Media Trial of Clarithromycin vs. Oral Cephalosporin

In a controlled clinical trial of pediatric patients with acute otitis media performed in the United States, where significant rates of beta-lactamase producing organisms were found, clarithromycin was compared to an oral cephalosporin. In this trial, strict evaluability criteria were used to determine clinical response. For the 223 patients who were evaluated for clinical efficacy, the clinical success rate (i.e., cure plus improvement) at the post-therapy visit was 88% for clarithromycin and 91% for the cephalosporin.

In a smaller number of patients, microbiologic determinations were made at the pre-treatment visit. The presumptive bacterial eradication/clinical cure outcomes (i.e., clinical success) are shown in Table 16.

Table 16. Clinical Success Rates of Otitis Media Treatment by Pathogen

Pathogen | Clinical Success Rates
Pathogen | Clarithromycin | Oral Cephalosporin
S. pneumoniae | 13/15 (87%) | 4/5
H. influenzae | 10/14 (71%) | 3/4
M. catarrhalis | 4/5 | 1/1
S. pyogenes | 3/3 | 0/1
All Pathogens Combined | 30/37 (81%) | 8/11 (73%)

Otitis Media Trials of Clarithromycin vs. Antimicrobial/Beta-lactamase Inhibitor

In two other controlled clinical trials of acute otitis media performed in the United States, where significant rates of beta-lactamase producing organisms were found, clarithromycin was compared to an oral antimicrobial agent that contained a specific beta-lactamase inhibitor. In these trials, strict evaluability criteria were used to determine the clinical responses. In the 233 patients who were evaluated for clinical efficacy, the combined clinical success rate (i.e., cure and improvement) at the post-therapy visit was 91% for both clarithromycin and the control.

For the patients who had microbiologic determinations at the pre-treatment visit, the presumptive bacterial eradication/clinical cure outcomes (i.e., clinical success) are shown in Table 17.

Table 17. Clinical Success Rates of Acute Otitis Media Treatment by Pathogen

PATHOGEN | Clinical Success Rates
PATHOGEN | Clarithromycin | Antimicrobial/Beta‑; lactamase Inhibitor
S. pneumoniae | 43/51 (84%) | 55/56 (98%)
H. influenzae | 36/45 (80%) | 31/33 (94%)
M. catarrhalis | 9/10 (90%) | 6/6
S. pyogenes | 3/3 | 5/5
All Pathogens Combined | 91/109 (83%) | 97/100 (97%)

14.3 H. pylori Eradication to Decrease the Risk of Duodenal Ulcer Recurrence

Clarithromycin + Lansoprazole and Amoxicillin

Two U.S. randomized, double-blind clinical trials (trial 6 and trial 7) in patients with H. pylori and duodenal ulcer disease (defined as an active ulcer or history of an active ulcer within one year) evaluated the efficacy of clarithromycin 500 mg twice daily in combination with lansoprazole 30 mg twice daily and amoxicillin 1 gm twice daily as 14-day triple therapy for eradication of H. pylori.

H. pylori eradication was defined as two negative tests (culture and histology) at 4 weeks to 6 weeks following the end of treatment.

The combination of clarithromycin plus lansoprazole and amoxicillin as triple therapy was effective in eradication of H. pylori (see results in Table 18). Eradication of H. pylori has been shown to reduce the risk of duodenal ulcer recurrence.

A randomized, double-blind clinical trial (trial 8) performed in the U.S. in patients with H. pylori and duodenal ulcer disease (defined as an active ulcer or history of an ulcer within one year) compared the efficacy of clarithromycin in combination with lansoprazole and amoxicillin as triple therapy for 10 days and 14 days. This trial established that the 10-day triple therapy was equivalent to the 14-day triple therapy in eradicating H. pylori (see results in Table 18).

Table 18. H. pylori Eradication Rates-Triple Therapy (clarithromycin/lansoprazole/amoxicillin) Percent of Patients Cured [95% Confidence Interval] (number of patients)

Trial | Duration | Triple Therapy; Evaluable Analysis | Triple Therapy; Intent-to-Treat Analysis†
Trial 6 | 14 days | 92‡ [80-97.7] (n = 48) | 86‡ [73.3-93.5] (n = 55)
Trial 7 | 14 days | 86§ [75.7-93.6] (n = 66) | 83§ [72-90.8] (n = 70)
Trial 8¶ | 14 days | 85 [77-91] (N = 113) | 82 [73.9-88.1] (N = 126)
 | 10 days | 84 [76-89.8] (N = 123) | 81 73.9-87.6] (N = 135)

Clarithromycin + Omeprazole and Amoxicillin Therapy

Three U.S., randomized, double-blind clinical trials in patients with H. pylori infection and duodenal ulcer disease (n = 558) compared clarithromycin plus omeprazole and amoxicillin to clarithromycin plus amoxicillin. Two trials (trials 9 and 10) were conducted in patients with an active duodenal ulcer, and the third trial (trial 11) was conducted in patients with a duodenal ulcer in the past 5 years, but without an ulcer present at the time of enrollment. The dosage regimen in the trials was clarithromycin 500 mg twice a day plus omeprazole 20 mg twice a day plus amoxicillin 1 gram twice a day for 10 days. In trials 9 and 10, patients who took the omeprazole regimen also received an additional 18 days of omeprazole 20 mg once a day. Endpoints studied were eradication of H. pylori and duodenal ulcer healing (trials 9 and 10 only). H. pylori status was determined by CLOtest®, histology, and culture in all three trials. For a given patient, H. pylori was considered eradicated if at least two of these tests were negative, and none was positive. The combination of clarithromycin plus omeprazole and amoxicillin was effective in eradicating H. pylori (see results in Table 19).

Table 19. H. pylori Eradication Rates: % of Patients Cured [95% Confidence Interval]

 | Clarithromycin + omeprazole + amoxicillin |  | Clarithromycin + amoxicillin
 | Per-Protocol | Intent-to-Treat† | Per-Protocol | Intent-to-Treat†
Trial 9 | ‡77 [64, 86] (n = 64) | 69 [57, 79] (n = 80) | 43 [31, 56] (n = 67) | 37 [27,48] (n =84)
Trial 10 | ‡78 [67, 88] (n = 65) | 73 [61, 82] (n = 77) | 41 [29, 54] (n = 68) | 36 [26, 47] (n =84)
Trial 11 | ‡90 [80, 96] (n = 69) | 83 [74, 91] (n = 84) | 33 [24, 44] (n = 93) | 32 23, 42] (n =99)

Clarithromycin + Omeprazole Therapy

Four randomized, double-blind, multi-center trials (trials 12, 13, 14, and 15) evaluated clarithromycin 500 mg three times a day plus omeprazole 40 mg once a day for 14 days, followed by omeprazole 20 mg once a day (trials 12, 13, and 15) or by omeprazole 40 mg once a day (trial 14) for an additional 14 days in patients with active duodenal ulcer associated with H. pylori. Trials 12 and 13 were conducted in the U.S. and Canada and enrolled 242 and 256 patients, respectively. H. pylori infection and duodenal ulcer were confirmed in 219 patients in trial 12 and 228 patients in trial 13. These trials compared the combination regimen to omeprazole and clarithromycin monotherapies. Trials 14 and 15were conducted in Europe and enrolled 154 and 215 patients, respectively. H. pylori infection and duodenal ulcer were confirmed in 148 patients in trial 14 and 208 patients in trial 15. These trials compared the combination regimen to omeprazole monotherapy. The results for the efficacy analyses for these trials are described in Tables 20, 21, and 22.

Duodenal Ulcer Healing

The combination of clarithromycin and omeprazole was as effective as omeprazole alone for healing duodenal ulcer (see Table 20).

Table 20. End-of-Treatment Ulcer Healing Rates Percent of Patients Healed (n/N)

Trial | Clarithromycin + Omeprazole | Omeprazole | Clarithromycin
U.S. Trials
Trial 13 | 94% (58/62)* | 88% (60/68) | 71% (49/69)
Trial 12 | 88% (56/64)* | 85% (55/65) | 64% (44/69)
Non-U.S. Trials
Trial 15 | 99% (84/85) | 95% (82/86) | N/A
Trial 14† | 100% (64/64) | 99% (71/72) | N/A

Eradication of H. pylori Associated with Duodenal Ulcer

The combination of clarithromycin and omeprazole was effective in eradicating H. pylori (see Table 21). H. pylori eradication was defined as no positive test (culture or histology) at 4 weeks following the end of treatment, and two negative tests were required to be considered eradicated. In the per-protocol analysis, the following patients were excluded: dropouts, patients with major protocol violations, patients with missing H. pylori tests post-treatment, and patients that were not assessed for H. pylori eradication at 4 weeks after the end of treatment because they were found to have an unhealed ulcer at the end of treatment.

Table 21. H. pylori Eradication Rates (Per-Protocol Analysis) at 4 to 6 weeks Percent of Patients Cured (n/N)

Trial | Clarithromycin + Omeprazole | Omeprazole | Clarithromycin
U.S. Trials
Trial 13 | 64% (39/61)* † | 0% (0/59) | 39% (17/44)
Trial 12 | 74% (39/53)* † | 0% (0/54) | 31% (13/42)
Non-U.S. Trials
Trial 15 | 74% (64/86)† | 1% (1/90) | N/A
Trial 14 | 83% (50/60)† | 1% (1/74) | N/A

Duodenal Ulcer Recurrence

Ulcer recurrence at 6-months and at 12 months following the end of treatment was assessed for patients in whom ulcers were healed post-treatment (see the results in Table 22). Thus, in patients with duodenal ulcer associated with H. pylori infection, eradication of H. pylori reduced ulcer recurrence.

Table 22. Duodenal Ulcer Recurrence at 6 months and 12 months in Patients with Healed Ulcers

 | H. pylori Negative at 4-6 Weeks | H. pylori Positive at 4-6 Weeks
U.S. Trials
Recurrence at 6 Months
Trial 100
Clarithromycin + Omeprazole | 6% (2/34) | 56% (9/16)
Omeprazole | (0/0) | 71% (35/49)
Clarithromycin | 12% (2/17) | 32% (7/22)
Trial 067
Clarithromycin + Omeprazole | 38% (11/29) | 50% (6/12)
Omeprazole | (0/0) | 67% (31/46)
Clarithromycin | 18% (2/11) | 52% (14/27)
Non-U.S. Trials
Recurrence at 6 Months
Trial 058
Clarithromycin + Omeprazole | 6% (3/53) | 24% (4/17)
Omeprazole | 0% (0/3) | 55% (39/71)
Trial 812b
Clarithromycin + Omeprazole | 5% (2/42) | 0% (0/7)
Omeprazole | 0% (0/1) | 54% (32/59)
Non-U.S. Trials
Recurrence at 12-Months in Trial 14
Clarithromycin + Omeprazole | 3% (1/40) | 0% (0/6)
Omeprazole | 0% (0/1) | 67% (29/43)

15 REFERENCES

1. Winkel P, Hilden J, Hansen JF, Kastrup J, Kolmos HJ, Kjøller E, et al. Clarithromycin for stable coronary heart disease increases all-cause and cardiovascular mortality and cerebrovascular morbidity over 10 years in the CLARICOR randomised, blinded clinical trial. Int J Cardiol 2015; 182:459-65.
2. Kemper CA, et al. Treatment of Mycobacterium avium Complex Bacteremia in AIDS with a Four-Drug Oral Regimen. Ann Intern Med. 1992;116:466-472.

16 HOW SUPPLIED/STORAGE AND HANDLING

Product: 50090-0994

NDC: 50090-0994-0 50 mL in a BOTTLE

17 PATIENT COUNSELING INFORMATION

Provide the following instructions or information about clarithromycin to patients:

Important Administration Instructions

Advise patients that clarithromycin for oral suspension can be taken with or without food and can be taken with milk. Do not refrigerate the suspension.

Drug Interactions

Advise patients that clarithromycin may interact with some drugs; therefore, advise patients to report to their healthcare provider the use of any other medications.

Diarrhea

Advise patients that diarrhea is a common problem caused by antibacterials including clarithromycin which usually ends when the antibacterial is discontinued. Sometimes after starting treatment with antibacterials, patients can develop watery and bloody stools (with or without stomach cramps and fever) even as late as two or more months after having taken the last dose of the antibacterial. If this occurs, instruct patients to contact their healthcare provider as soon as possible.

Embryo-fetal Toxicity

Advise females of reproductive potential that if pregnancy occurs while taking this drug, there is a potential hazard to the fetus [see Warnings and Precautions (5.7) and Use in Specific Populations (8.1)].

Antibacterial Resistance

Counsel patients that antibacterial drugs including clarithromycin should only be used to treat bacterial infections. They do not treat viral infections (e.g., the common cold). When clarithromycin is prescribed to treat a bacterial infection, patients should be told that although it is common to feel better early in the course of therapy, the medication should be taken exactly as directed. Skipping doses or not completing the full course of therapy may (1) decrease the effectiveness of the immediate treatment and (2) increase the likelihood that bacteria will develop resistance and will not be treatable by clarithromycin or other antibacterial drugs in the future.

Potential for Dizziness, Vertigo and Confusion

There are no data on the effect of clarithromycin on the ability to drive or use machines. However, counsel patients regarding the potential for dizziness, vertigo, confusion and disorientation, which may occur with the clarithromycin. The potential for these adverse reactions should be taken into account before patients drive or use machines.

Risk of Mortality in Patients with Coronary Disease Years After Clarithromycin Treatment

Advise patients who have coronary artery disease to continue medications and lifestyle modifications for their coronary artery disease because clarithromycin may be associated with increased risk for mortality years after the end of clarithromycin treatment.

Manufactured in Romania by Sandoz SRL for

Sandoz Inc., Princeton, NJ 08540

Rev. September 2023